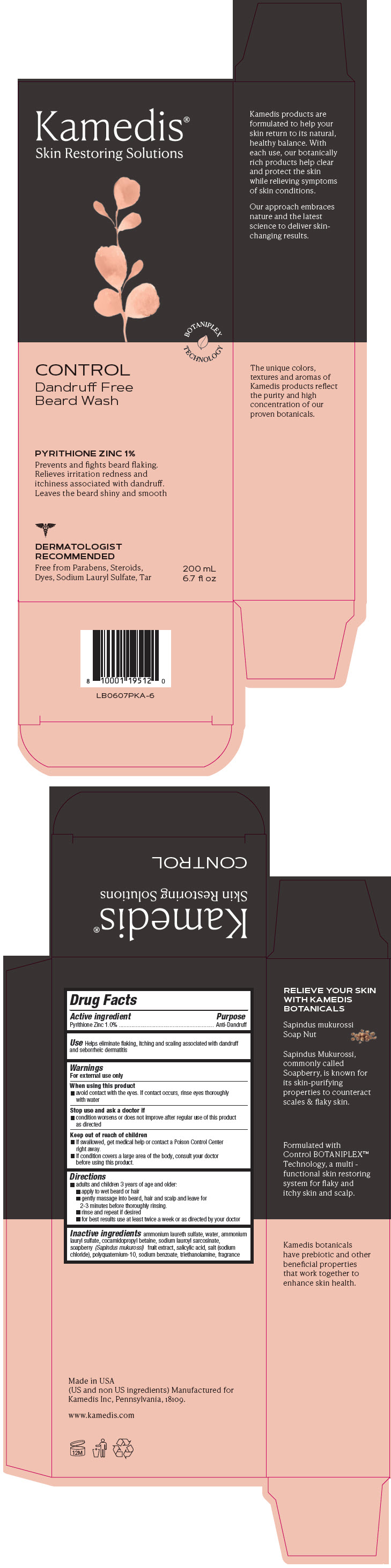 DRUG LABEL: CONTROL Dandruff- Free Beard Wash
NDC: 50718-0035 | Form: SHAMPOO
Manufacturer: Kamedis Inc
Category: otc | Type: HUMAN OTC DRUG LABEL
Date: 20231127

ACTIVE INGREDIENTS: PYRITHIONE ZINC 10 mg/1 mL
INACTIVE INGREDIENTS: AMMONIUM LAURYL SULFATE; COCAMIDOPROPYL BETAINE; SALICYLIC ACID; SODIUM CHLORIDE; SAPINDUS MUKOROSSI FRUIT; SODIUM BENZOATE; SODIUM LAUROYL SARCOSINATE; WATER; AMMONIUM LAURETH-2 SULFATE; POLYQUATERNIUM-10 (10000 MPA.S AT 2%); TROLAMINE

CONTROL Dandruff- Free Beard Wash

Drug Facts

Active ingredient

Pyrithione Zinc 1.0%

Purpose

Anti-Dandruff

Use

Helps eliminate flaking, itching and scaling associated with dandruff and seborrheic dermatitis

Warnings

For external use only

When using this product

- avoid contact with the eyes. If contact occurs, rinse eyes thoroughly with water

Stop use and ask a doctor if

- condition worsens or does not improve after regular use of this product as directed

Keep out of reach of children

- If swallowed, get medical help or contact a Poison Control Center right away.
- If condition covers a large area of the body, consult your doctor before using this product.

Directions

- adults and children 3 years of age and older:
  - apply to wet beard or hair
  - gently massage into beard, hair and scalp and leave for 2-3 minutes before thoroughly rinsing.
  - rinse and repeat if desired
  - for best results use at least twice a week or as directed by your doctor

Inactive ingredients

ammonium laureth sulfate, water, ammonium lauryl sulfate, cocamidopropyl betaine, sodium lauroyl sarcosinate, soapberry (Sapindus mukurossi) fruit extract, salicylic acid, salt (sodium chloride), polyquaternium-10, sodium benzoate, triethanolamine, fragrance

PRINCIPAL DISPLAY PANEL - 200 mL Bottle Carton

Kamedis®
Skin Restoring Solutions

BOTANIPLEX
TECHNOLOGY

CONTROL
Dandruff Free
Beard Wash

PYRITHIONE ZINC 1%
Prevents and fights beard flaking.
Relieves irritation redness and
itchiness associated with dandruff.
Leaves the beard shiny and smooth

DERMATOLOGIST
RECOMMENDED
Free from Parabens, Steroids,
Dyes, Sodium Lauryl Sulfate, Tar

200 mL
6.7 fl oz